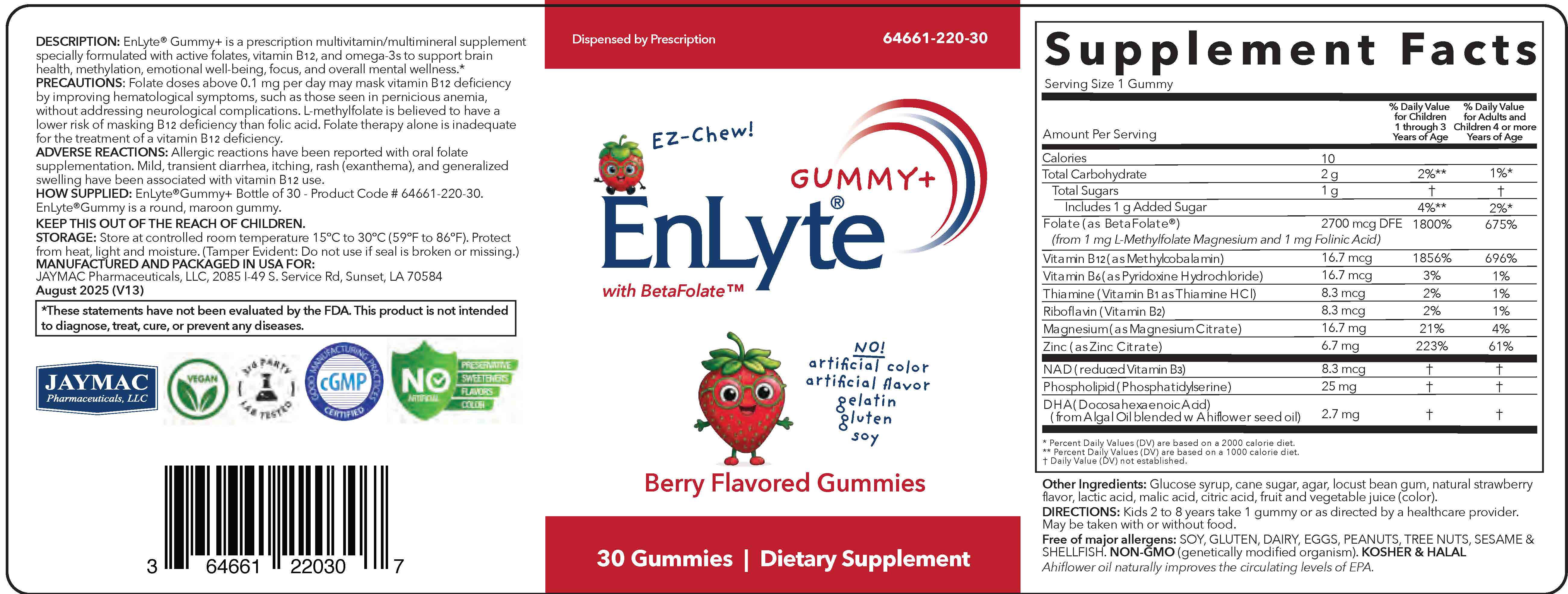 DRUG LABEL: EnLyte Gummy plus
NDC: 64661-220 | Form: CHEWABLE GEL
Manufacturer: Jaymac Pharma
Category: other | Type: Dietary Supplement
Date: 20251210

ACTIVE INGREDIENTS: LEVOMEFOLATE MAGNESIUM 1 mg/1 1; LEUCOVORIN 1 mg/1 1; METHYLCOBALAMIN 16.7 ug/1 1; ZINC CITRATE 6.7 mg/1 1; MAGNESIUM CITRATE 16.7 mg/1 1; PYRIDOXINE HYDROCHLORIDE 16.7 ug/1 1; THIAMINE HCL 8.3 ug/1 1; RIBOFLAVIN 8.3 ug/1 1; PHOSPHATIDYLSERINE 25 mg/1 1; NICOTINAMIDE ADENINE DINUCLEOTIDE 8.3 ug/1 1; DOCOSAHEXAENOIC ACID ALGAL OIL 2.7 mg/1 1
INACTIVE INGREDIENTS: GLUCOSE; SUCROSE; AGAR; LOCUST BEAN GUM; LACTIC ACID; MALIC ACID; CITRIC ACID; STRAWBERRY; BUGLOSSOIDES ARVENSIS WHOLE

EnLyte® Gummy+
with BetaFolate™

STATEMENT OF IDENTITY

DIETARY SUPPLEMENT

DESCRIPTION:

EnLyte® Gummy+ is a prescription multivitamin/multimineral supplement specially formulated with active folates, vitamin B12, and omega-3s to support brain health, methylation, emotional well-being, focus, and overall mental wellness.*

Free of major allergens: SOY, GLUTEN, DAIRY, EGGS, PEANUTS, TREE NUTS, SESAME & SHELLFISH.

No artificial colors, artificial flavor, gelatin.

NON-GMO (genetically modified organism).

KOSHER & HALAL

Ahiflower oil naturally improves the circulating levels of EPA.

*These statements have not been evaluated by the FDA. This product is not intended to diagnose, treat, cure, or prevent any diseases.

DIRECTIONS:

Kids 2 to 8 years take 1 gummy or as directed by a healthcare provider. May be taken with or without food.

PRECAUTIONS:

Folate doses above 0.1 mg per day may mask vitamin B12 deficiency by improving hematological symptoms, such as those seen in pernicious anemia, without addressing neurological complications. L-methylfolate is believed to have a lower risk of masking B12 deficiency than folic acid. Folate therapy alone is inadequate for the treatment of a vitamin B12 deficiency.
ADVERSE REACTIONS:

Allergic reactions have been reported with oral folate supplementation. Mild, transient diarrhea, itching, rash (exanthema), and generalized swelling have been associated with vitamin B12 use

HOW SUPPLIED:

EnLyte®Gummy+ Bottle of 30 - Product Code # 64661-220-30. EnLyte®Gummy+ is a round, maroon gummy.

STORAGE:

Store at controlled room temperature 15°C to 30°C (59°F to 86°F). Protect from heat, light, and moisture. (Tamper Evident: Do not use if seal is broken or missing.)

WARNING:

KEEP THIS OUT OF THE REACH OF CHILDREN.